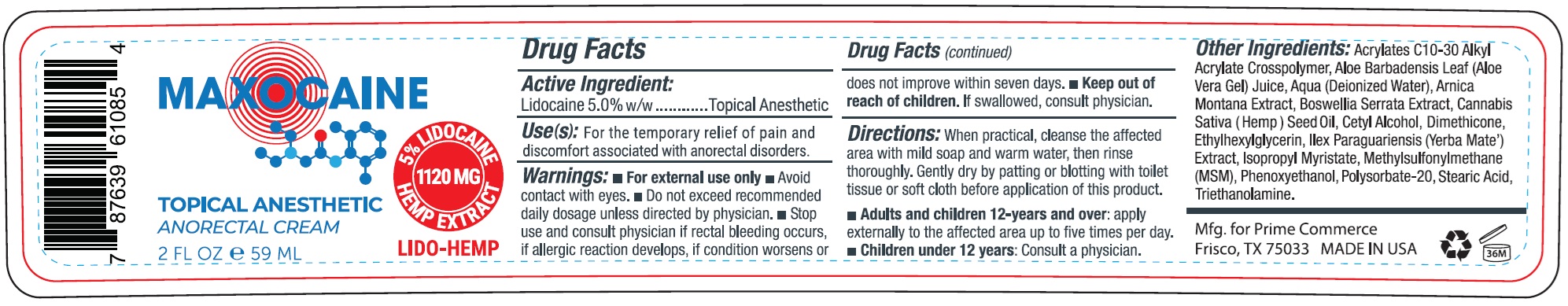 DRUG LABEL: MAXOCAINE Topical Anesthetic Anorectal
NDC: 72188-076 | Form: CREAM
Manufacturer: PRIME COMMERCE, LLC
Category: otc | Type: HUMAN OTC DRUG LABEL
Date: 20250527

ACTIVE INGREDIENTS: LIDOCAINE 50 mg/1 mL
INACTIVE INGREDIENTS: CARBOMER INTERPOLYMER TYPE A (ALLYL SUCROSE CROSSLINKED); ALOE VERA LEAF; WATER; ARNICA MONTANA WHOLE; INDIAN FRANKINCENSE; CANNABIS SATIVA SEED OIL; CETYL ALCOHOL; DIMETHICONE; ETHYLHEXYLGLYCERIN; ILEX PARAGUARIENSIS LEAF; ISOPROPYL MYRISTATE; DIMETHYL SULFONE; PHENOXYETHANOL; POLYSORBATE 20; STEARIC ACID; TROLAMINE

MAXOCAINE Topical Anesthetic Anorectal

Active Ingredient:

Lidocaine 5.0% w/w

Purpose

Topical Anesthetic

Use(s):

For the temporary relief of pain and discomfort associated with anorectal disorders.

Warnings:

- For external use only
- Avoid contact with eyes.
- Do not exceed recommended daily dosage unless directed by physician.

Stop use and consult physician

if rectal bleeding occurs, if allergic reaction develops, if condition worsens or does not improve within seven days.

Keep out of reach of children.

If swallowed, consult physician.

Directions:

When practical, cleanse the affected area with mild soap and warm water, then rinse thoroughly. Gently dry by patting or blotting with toilet tissue or soft cloth before application of this product.

- Adults and children 12-years and over:apply externally to the affected area up to five times per day.
- Children under 12-years:Consult a physician.

Other Ingredients:

Acrylates C10-30 Alkyl Acrylate Crosspolymer, Aloe Barbadensis Leaf (Aloe Vera Gel) Juice, Aqua (Deionzied Water), Arnica Montana Extract, Boswellia Serrata Extract, Cannabis Sativa (Hemp) Seed Oil, Cetyl Alcohol, Dimethicone, Ethylhexylglycerin, Ilex Paraguariensis (Yerba Mate) Extract, Isopropyl Myristate, methylsulfonylmethane (MSM), Phenoxyethanol, Polysorbate-20, Stearic Acid, Triethanolamine.